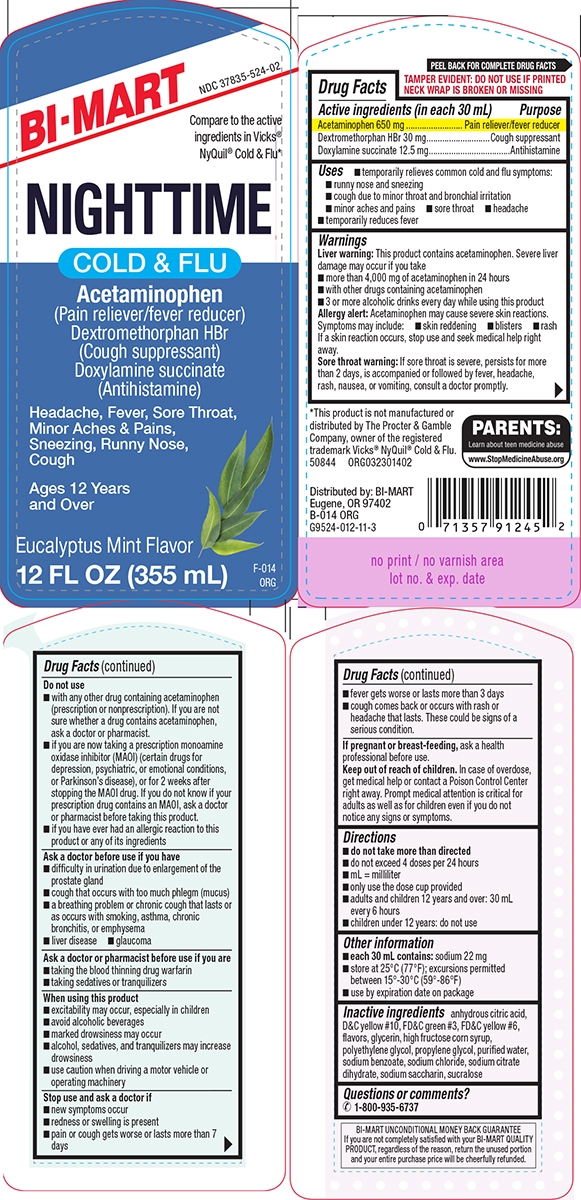 DRUG LABEL: Cold and Flu
NDC: 37835-524 | Form: SOLUTION
Manufacturer: Bi-Mart
Category: otc | Type: HUMAN OTC DRUG LABEL
Date: 20250710

ACTIVE INGREDIENTS: ACETAMINOPHEN 650 mg/30 mL; DEXTROMETHORPHAN HYDROBROMIDE 30 mg/30 mL; DOXYLAMINE SUCCINATE 12.5 mg/30 mL
INACTIVE INGREDIENTS: ANHYDROUS CITRIC ACID; D&C YELLOW NO. 10; FD&C GREEN NO. 3; FD&C YELLOW NO. 6; GLYCERIN; HIGH FRUCTOSE CORN SYRUP; POLYETHYLENE GLYCOL, UNSPECIFIED; PROPYLENE GLYCOL; WATER; SODIUM BENZOATE; SODIUM CHLORIDE; TRISODIUM CITRATE DIHYDRATE; SACCHARIN SODIUM; SUCRALOSE

Bi-Mart 44-014

Active ingredients (in each 30 mL)

Acetaminophen 650 mg
Dextromethorphan HBr 30 mg
Doxylamine succinate 12.5 mg

Purpose

Pain reliever/fever reducer
Cough suppressant
Antihistamine

Uses

- temporarily relieves common cold and flu symptoms:
  - runny nose and sneezing
  - cough due to minor throat and bronchial irritation
  - minor aches and pains
  - sore throat
  - headache
- temporarily reduces fever

Warnings

Liver warning: This product contains acetaminophen. Severe liver damage may occur if you take

- more than 4,000 mg of acetaminophen in 24 hours
- with other drugs containing acetaminophen
- 3 or more alcoholic drinks every day while using this product

Allergy alert: Acetaminophen may cause severe skin reactions. Symptoms may include:

- skin reddening
- blisters
- rash

If a skin reaction occurs, stop use and seek medical help right away.

Sore throat warning: If sore throat is severe, persists for more than 2 days, is accompanied or followed by fever, headache, rash, nausea, or vomiting, consult a doctor promptly.

Do not use

- with any other drug containing acetaminophen (prescription or nonprescription). If you are not sure whether a drug contains acetaminophen, ask a doctor or pharmacist.
- if you are now taking a prescription monoamine oxidase inhibitor (MAOI) (certain drugs for depression, psychiatric, or emotional conditions, or Parkinson’s disease), or for 2 weeks after stopping the MAOI drug. If you do not know if your prescription drug contains an MAOI, ask a doctor or pharmacist before taking this product.
- if you have ever had an allergic reaction to this product or any of its ingredients

Ask a doctor before use if you have

- difficulty in urination due to enlargement of the prostate gland
- cough that occurs with too much phlegm (mucus)
- a breathing problem or chronic cough that lasts or as occurs with smoking, asthma, chronic bronchitis, or emphysema
- liver disease
- glaucoma

Ask a doctor or pharmacist before use if you are

- taking the blood thinning drug warfarin
- taking sedatives or tranquilizers

When using this product

- excitability may occur, especially in children
- avoid alcoholic beverages
- marked drowsiness may occur
- alcohol, sedatives, and tranquilizers may increase drowsiness
- use caution when driving a motor vehicle or operating machinery

Stop use and ask a doctor if

- pain or cough gets worse or lasts more than 7 days
- fever gets worse or lasts more than 3 days
- redness or swelling is present
- new symptoms occur
- cough comes back or occurs with rash or headache that lasts. These could be signs of a serious condition.

If pregnant or breast-feeding,

ask a health professional before use.

Keep out of reach of children.

In case of overdose, get medical help or contact a Poison Control Center right away. Prompt medical attention is critical for adults as well as for children even if you do not notice any signs or symptoms.

Directions

- do not take more than directed
- do not exceed 4 doses per 24 hours
- mL = milliliter
- only use the dose cup provided
- adults and children 12 years and over: 30 mL every 6 hours
- children under 12 years: do not use

Other information

- each 30 mL contains: sodium 22 mg
- store at 25°C (77°F); excursions permitted between 15°-30°C (59°-86°F)
- use by expiration date on package

Inactive ingredients

anhydrous citric acid, D&C yellow #10, FD&C green #3, FD&C yellow #6, flavors, glycerin, high fructose corn syrup, polyethylene glycol, propylene glycol, purified water, sodium benzoate, sodium chloride, sodium citrate dihydrate, sodium saccharin, sucralose

Questions or comments?

1-800-935-6737

Principal Display Panel

BI-MART

NDC 37835-524-02

Compare to the active
ingredients in Vicks®
NyQuil® Cold & Flu*

NIGHTTIME
COLD & FLU

Acetaminophen
(Pain reliever/fever reducer)
Dextromethorphan HBr
(Cough suppressant)
Doxylamine succinate
(Antihistamine)

Headache, Fever, Sore Throat,
Minor Aches & Pains,
Sneezing, Runny Nose,
Cough

Ages 12 Years
and Over

Eucalyptus Mint Flavor

12 FL OZ (355 mL)

TAMPER EVIDENT: DO NOT USE IF PRINTED
NECK WRAP IS BROKEN OR MISSING

PARENTS:
Learn About Teen Medicine Abuse
www.StopMedicineAbuse.org

BI-MART UNCONDITIONAL MONEY BACK GUARANTEE
If you are not completely satisfied with your BI-MART QUALITY
PRODUCT, regardless of the reason, return the unused portion
and your entire purchase price will be cheerfully refunded.

*This product is not manufactured or
distributed by The Procter & Gamble
Company, owner of the registered
trademark Vicks® NyQuil® Cold & Flu.
50844 ORG032301402

Distributed by: BI-MART
Eugene, OR 97402
B-014 ORG
G9524-012-11-3

BiMart 44-014